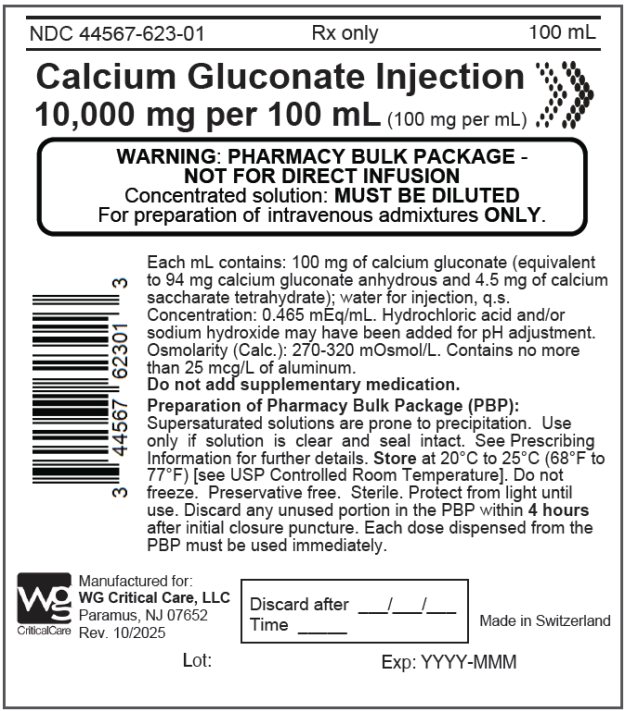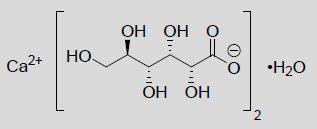 DRUG LABEL: Calcium Gluconate
NDC: 44567-623 | Form: INJECTION, SOLUTION
Manufacturer: WG Critical Care, LLC
Category: prescription | Type: HUMAN PRESCRIPTION DRUG LABEL
Date: 20260217

ACTIVE INGREDIENTS: CALCIUM GLUCONATE 100 mg/1 mL
INACTIVE INGREDIENTS: HYDROCHLORIC ACID; SODIUM HYDROXIDE

HIGHLIGHTS OF PRESCRIBING INFORMATION

These highlights do not include all the information needed to use CALCIUM GLUCONATE INJECTION safely and effectively. See full prescribing information for CALCIUM GLUCONATE INJECTION.
CALCIUM GLUCONATE injection, for intravenous use
Initial U.S. Approval: 1941

1 INDICATIONS AND USAGE

• Calcium Gluconate Injection is a form of calcium indicated for pediatric and adult patients for the treatment of acute symptomatic hypocalcemia. (1)

• Limitations of Use: The safety of Calcium Gluconate Injection for long term use has not been established. (1)

2 DOSAGE AND ADMINISTRATION

• Pharmacy Bulk Package: Not for direct intravenous infusion (2.1)

• Administer intravenously (bolus or continuous infusion) via a secure intravenous line (2.1)

• See Full Prescribing Information (FPI) for dilution instructions, administration rates, and appropriate monitoring (2.1)

• Individualize the dose within the recommended range in adults and pediatric patients depending on the severity of symptoms of hypocalcemia, the serum calcium level, and the acuity of onset of hypocalcemia. See Table 1 in the FPI for dosing recommendations in mg of calcium gluconate for neonates, pediatric and adult patients. (2.2)

• Measure serum calcium during intermittent infusions every 4 to 6 hours and during continuous infusion every 1 to 4 hours. (2.3)

• Calcium Gluconate Injection is not physically compatible with fluids containing phosphate or bicarbonate. Precipitation may result if mixed. See FPI for all drug incompatibilities. (2.5)

• Supplied in a pharmacy bulk package for use in a pharmacy admixture program. Use within 4 hours of puncture (2.6)

3 DOSAGE FORMS AND STRENGTHS

Injection: (3)

• Pharmacy Bulk Package (bag): 10,000 mg per 100 mL (100 mg per mL)

4 CONTRAINDICATIONS

• Hypercalcemia (4)

• Neonates (28 days of age or younger) receiving ceftriaxone (4)

5 WARNINGS AND PRECAUTIONS

• Arrhythmias with Concomitant Cardiac Glycoside Use: If concomitant therapy is necessary, calcium gluconate injection should be given slowly in small amounts and close ECG monitoring is recommended (5.1)

• End-Organ Damage due to Intravascular Ceftriaxone-Calcium Precipitates: Concurrent use of intravenous ceftriaxone may cause life-threatening precipitates. Do not administer ceftriaxone simultaneously with Calcium Gluconate Injection via a Y-site in any age group. Cases of fatal outcomes in neonates have occurred. (4, 5.2)

• Tissue Necrosis and Calcinosis: Calcinosis cutis can occur with or without extravasation of calcium gluconate injection. Tissue necrosis, ulceration, and secondary infection are the most serious complications. If extravasation occurs or clinical manifestations of calcinosis cutis are noted, immediately discontinue intravenous administration at that site and treat as needed. (5.3)

• Hypotension, Bradycardia, and Cardiac Arrhythmias with Rapid Administration: To avoid adverse reactions that may follow rapid intravenous administration, calcium gluconate injection should be diluted with 5% dextrose or normal saline and infused slowly, with careful ECG monitoring for cardiac arrhythmias. (5.4)

• Aluminum Toxicity: This product contains aluminum, up to 25 mcg per liter, that may be toxic. (5.5)

6 ADVERSE REACTIONS

The most common adverse events with calcium gluconate injection are local soft tissue inflammation and necrosis, calcinosis cutis and calcification that are related to extravasation. Other adverse events include vasodilation, decreased blood pressure, bradycardia, cardiac arrhythmia, syncope, and cardiac arrest. (6)

To report SUSPECTED ADVERSE REACTIONS, contact WG Critical Care, LLC at 1-866-562-4708 or FDA at 1-800-FDA-1088 or www.fda.gov/medwatch.

7 DRUG INTERACTIONS

• Cardiac Glycoside: Synergistic arrhythmias may occur if calcium and cardiac glycosides are administered together. (7.1)

• Calcium Channel Blockers: Administration of calcium may reduce the response. (7.2)

• Drugs that may cause hypercalcemia: Vitamin D, vitamin A, thiazide diuretics, estrogen, calcipotriene and teriparatide administration may cause hypercalcemia. Monitor plasma calcium concentrations in patients taking these drugs concurrently. (7.3)

8 USE IN SPECIFIC POPULATIONS

• Geriatric Use: Dosing in elderly patients should be cautious, usually starting at the low end of the dosage range. (8.5)

• Renal Impairment: Initiate with the lower limit of the dosage range and monitor serum calcium levels every 4 hours. (8.6, 2.4)

FULL PRESCRIBING INFORMATION

1 INDICATIONS AND USAGE

Calcium Gluconate Injection is indicated for pediatric and adult patients for the treatment of acute symptomatic hypocalcemia.

Limitations of Use

The safety of Calcium Gluconate Injection for long term use has not been established.

2 DOSAGE AND ADMINISTRATION

2.1 Important Administration Instructions

- Calcium Gluconate Injection 10,000 mg per 100 mL (100 mg per mL) is supplied as a pharmacy bulk package for admixing use only. It is not for direct intravenous infusion.
- Calcium Gluconate Injection contains 100 mg of calcium gluconate per mL which contains 9.3 mg (i.e., 0.465 mEq) of elemental calcium.
- Prior to use, dilute Calcium Gluconate Injection in 5% dextrose or normal saline and assess for potential drug or IV fluid incompatibilities [see Dosage and Administration (2.5, 2.6)].
- Inspect Calcium Gluconate Injection visually prior to administration. The solution should appear clear and colorless. Do not administer if there is particulate matter or discoloration.
- Administer Calcium Gluconate Injection intravenously via a secure intravenous line to avoid calcinosis cutis and tissue necrosis [see Warnings and Precautions (5.3)].
- Administer diluted Calcium Gluconate Injection by bolus administration or continuous infusion at the rate recommended in Table 1 [see Dosage and Administration (2.2)]
- Monitor patients, vitals, calcium and ECG during the infusion [see Warnings and Precautions (5.4)]

2.2 Recommended Dosage and Administration

Individualize the dose of Calcium Gluconate Injection within the recommended range depending on the severity of symptoms of hypocalcemia, the serum calcium level, and the acuity of onset of hypocalcemia.

Table 1 provides dosing recommendations for Calcium Gluconate Injection in mg of calcium gluconate for neonates, pediatric and adult patients.

Table 1. Recommended Dosage of Calcium Gluconate for Neonate, Pediatric, and Adult Patients

Patient Population |  | Subsequent Doses (if needed)
Patient Population |  | Bolus* | Continuous Infusion+
Neonate (≤ 1 month) | 100 mg/kg to 200 mg/kg | 100 mg/kg to 200 mg/kg every 6 hours | Initiate at 17 mg/kg/hour to 33 mg/kg/hour
Pediatric (> 1 month to < 17 years) | 29 mg/kg to 60 mg/kg | 29 mg/kg to 60 mg/kg every 6 hours | Initiate at 8 mg/kg/hour to 13 mg/kg/hour
Adult (≥ 17 years) | 1000 mg to 2000 mg | 1000 mg to 2000 mg every 6 hours | Initiate at 5.4 mg/kg/hour to 21.5 mg/kg/hour
*For bolus administration, DO NOT exceed an infusion rate of:
•200 mg/minute in adult patients
•100 mg/minute in pediatric patients
+For continuous infusions, adjust rate as needed based on serum calcium levels

For Bolus Intravenous Administration

- Administer the bolus slowly and do not exceed an infusion rate of 200 mg/minute in adults or 100 mg/minute in pediatric patients, including neonates.
- Monitor patients, vitals and electrocardiograph (ECG) during administration [see Warnings and Precautions (5.4)].

For Continuous Intravenous Infusion

- Administer by continuous infusion at the rate recommended in Table 1.
- Adjust continuous infusion rate as needed based on serum calcium levels.
- Monitor patients, vitals, calcium and ECG during the infusion [see Warnings and Precautions (5.4)].

2.3 Serum Calcium Monitoring

Measure serum calcium every 4 to 6 hours during intermittent infusions with Calcium Gluconate Injection and measure serum calcium every 1 to 4 hours during continuous infusion.

2.4 Dosage in Renal Impairment

For patients with renal impairment, initiate Calcium Gluconate Injection at the lowest dose of the recommended dose ranges for all age groups and monitor serum calcium levels every 4 hours.

2.5 Drug Incompatibilities

- Do not mix Calcium Gluconate Injection with ceftriaxone. Concurrent use of intravenous ceftriaxone and Calcium Gluconate Injection can lead to the formation of ceftriaxone-calcium precipitates. Concomitant use of ceftriaxone and intravenous calcium-containing products is contraindicated in neonates (28 days of age or younger) [see Contraindications (4)]. In patients older than 28 days of age, ceftriaxone and calcium-containing products may be administered sequentially, provided the infusion lines are thoroughly flushed between infusions with a compatible fluid. Ceftriaxone must not be administered simultaneously with intravenous calcium-containing solutions via a Y-site in any age group [see Warnings and Precautions (5.2), Drug Interactions (7.3)].
- Do not mix Calcium Gluconate Injection with fluids containing bicarbonate or phosphate. Calcium Gluconate Injection is not physically compatible with fluids containing phosphate or bicarbonate. Precipitation may result if mixed.
- Do not mix Calcium Gluconate Injection with minocycline injection. Calcium complexes minocycline rendering it inactive.

2.6 Preparation and Storage of Pharmacy Bulk Package

- The pharmacy bulk package of Calcium Gluconate Injection is intended for dispensing of single doses to multiple patients in a pharmacy admixture program.
- Transfer Calcium Gluconate Injection from the Pharmacy Bulk Package in an aseptic work area such as a laminar flow hood (or an equivalent clean air compounding area) and using aseptic technique.
- Penetrate the container closure only one time with a suitable sterile transfer device or dispensing set that allows measured dispensing of the contents.
- For Bolus Intravenous Administration, dilute the volume containing the recommended dosage of Calcium Gluconate Injection in 5% dextrose or normal saline to a concentration of 10 mg/mL to 50 mg/mL prior to administration.
- For Continuous Intravenous Infusion, dilute the volume containing the recommended dosage of Calcium Gluconate Injection in 5% dextrose or normal saline to a concentration of 5.8 mg/mL to 10 mg/mL prior to administration.
- Dispense Calcium Gluconate Injection from the Pharmacy Bulk Package within 4 hours after the container closure is penetrated. Each dose dispensed from the Pharmacy Bulk Package must be used immediately.
- Do not add supplementary medication.
- Parenteral drug products should be inspected visually for particulate matter and discoloration prior to administration or admixture and final infusate should be inspected for cloudiness or precipitation immediately after mixing, prior to administration, and periodically during administration, whenever solution and container permit. Use of a final filter is recommended during administration of all parenteral solutions where possible.
- This solution is intended for use in the preparation of sterile, intravenous admixtures.
- Do not store any unused portion.

3 DOSAGE FORMS AND STRENGTHS

Calcium Gluconate Injection is a clear, colorless solution available in a Pharmacy Bulk Package (bag): 10,000 mg per 100 mL (100 mg per mL)

Each mL of Calcium Gluconate Injection contains 9.3 mg (0.465 mEq) of elemental calcium.

4 CONTRAINDICATIONS

Calcium gluconate injection is contraindicated in:

•Hyperca lcemia

• Neonates (28 days of age or younger) receiving ceftriaxone [see Warnings and Precautions (5.2)]

5 WARNINGS AND PRECAUTIONS

5.1 Arrhythmias with Concomitant Cardiac Glycoside Use

Cardiac arrhythmias may occur if calcium and cardiac glycosides are administered together. Hypercalcemia increases the risk of digoxin toxicity. Administration of calcium gluconate injection should be avoided in patients receiving cardiac glycosides. If concomitant therapy is necessary, calcium gluconate injection should be given slowly in small amounts and with close ECG monitoring [see Drug Interactions (7.1)].

5.2 End-Organ Damage due to Intravascular Ceftriaxone-Calcium Precipitates

Concomitant use of ceftriaxone and calcium gluconate injection is contraindicated in neonates (28 days of age or younger) due to cases of fatal outcomes in neonates in which a crystalline material was observed in the lungs and kidneys at autopsy after ceftriaxone and calcium were administrated simultaneously through the same intravenous line. Concomitant administration can lead to the formation of ceftriaxone-calcium precipitates that may act as emboli, resulting in vascular spasm or infarction [see Contraindications (4)].

In patients older than 28 days of age, ceftriaxone and calcium gluconate injection may be administered sequentially, provided the infusion lines are thoroughly flushed between infusions with a compatible fluid. Do not administer Ceftriaxone simultaneously with calcium gluconate injection via a Y-site in any age group.

5.3 Tissue Necrosis and Calcinosis

Intravenous administration of calcium gluconate injection and local trauma may result in calcinosis cutis due to transient increase in local calcium concentration. Calcinosis cutis can occur with or without extravasation of calcium gluconate injection, is characterized by abnormal dermal deposits of calcium salts, and clinically manifests as papules, plaques, or nodules that may be associated with erythema, swelling, or induration. Tissue necrosis, ulceration, and secondary infection are the most serious complications.

If extravasation occurs or clinical manifestations of calcinosis cutis are noted, immediately discontinue intravenous administration at that site and treat as needed.

5.4 Hypotension, Bradycardia, and Cardiac Arrhythmias with Rapid Administration

Rapid injection of calcium gluconate injection may cause vasodilation, decreased blood pressure, bradycardia, cardiac arrhythmias, syncope and cardiac arrest. To avoid adverse reactions that may follow rapid intravenous administration, Calcium gluconate injection should be diluted with 5% dextrose or normal saline and infused slowly. If rapid intravenous bolus of calcium gluconate injection is required, the rate of intravenous administration should not exceed 200 mg/minute in adults and 100 mg/minute in pediatric patients and ECG monitoring during administration is recommended [see Dosage and Administration (2.1)].

5.5 Aluminum Toxicity

Calcium gluconate injection contains aluminum, up to 25 mcg per liter, that may be toxic. Aluminum may reach toxic levels with prolonged parenteral administration if kidney function is impaired. Premature neonates are particularly at risk because their kidneys are immature, and they require large amounts of calcium and phosphate solutions, which contain aluminum. Research indicates that patients with impaired kidney function, including premature neonates, who receive parenteral levels of aluminum at greater than 4 mcg/kg/day to 5 mcg/kg/day accumulate aluminum levels associated with central nervous system and bone toxicity. Tissue loading may occur at even lower rates of administration.

6 ADVERSE REACTIONS

The following serious adverse reactions are also described elsewhere in the labeling:

• Arrhythmias with Concomitant Cardiac Glycoside Use [see Warnings and Precautions (5.1)]

• End-Organ Damage due to Intravascular Ceftriaxone-Calcium Precipitates [see Warnings and Precautions (5.2)]

• Tissue Necrosis and Calcinosis [see Warnings and Precautions (5.3)]

• Hypotension, Bradycardia, and Cardiac Arrhythmias [see Warnings and Precautions (5.4)]

• Aluminum toxicity [see Warnings and Precautions (5.5)]

The following adverse reactions associated with the use of calcium gluconate were identified in the literature. Because these reactions are reported voluntarily from a population of uncertain size, it is not always possible to estimate their frequency reliably or to establish a causal relationship to drug exposure.

Cardiovascular: Vasodilation, decreased blood pressure, bradycardia, cardiac arrhythmia, syncope, cardiac arrest

Administration site reactions: Local soft tissue inflammation, local necrosis, calcinosis cutis and calcification due to extravasation

7 DRUG INTERACTIONS

7.1 Cardiac Glycosides

Hypercalcemia increases the risk of digoxin toxicity, while digoxin may be therapeutically ineffective in the presence of hypocalcemia. Synergistic arrhythmias may occur if calcium and cardiac glycosides are administered together. Avoid administration of calcium gluconate injection in patients receiving cardiac glycosides; if considered necessary, administer calcium gluconate injection slowly in small amounts and monitor ECG closely during administration.

7.2 Calcium Channel Blockers

Administration of calcium may reduce the response to calcium channel blockers.

7.3 Drugs that may cause Hypercalcemia

Vitamin D, vitamin A, thiazide diuretics, estrogen, calcipotriene and teriparatide administration may cause hypercalcemia. Monitor plasma calcium concentrations in patients taking these drugs concurrently.

8 USE IN SPECIFIC POPULATIONS

8.1 Pregnancy

Risk summary

Limited available data with calcium gluconate injection use in pregnant women are insufficient to inform a drug associated risk of adverse developmental outcomes. There are risks to the mother and the fetus associated with hypocalcemia in pregnancy [see Clinical Considerations].

The estimated background risk of major birth defects and miscarriage for the indicated population is unknown. In the U.S. general population, the estimated background risk of major birth defects and miscarriage in clinically recognized pregnancies is 2-4% and 15-20%, respectively.

Clinical Considerations

Disease-associated maternal risk

Maternal hypocalcemia can result in an increased rate of spontaneous abortion, premature and dysfunctional labor, and possibly preeclampsia.

Fetal/Neonatal adverse reactions

Infants born to mothers with hypocalcemia can have associated fetal and neonatal hyperparathyroidism, which in turn can cause fetal and neonatal skeletal demineralization, subperiosteal bone resorption, osteitis fibrosa cystica and neonatal seizures. Infants born to mothers with hypocalcemia should be carefully monitored for signs of hypocalcemia or hypercalcemia, including neuromuscular irritability, apnea, cyanosis and cardiac rhythm disorders.

8.2 Lactation

Risk summary

Calcium is present in human milk as a natural component of human milk. It is not known whether intravenous administration of calcium gluconate injection can alter calcium concentration in human milk. There are no data on the effects of calcium gluconate injection on the breastfed infant, or on milk production. The developmental and health benefits of breastfeeding should be considered along with the mother’s clinical need for calcium gluconate injection and any potential adverse effects on the breastfed child from calcium gluconate injection or from the underlying maternal condition.

8.4 Pediatric Use

The safety and effectiveness of calcium gluconate injection have been established in pediatric patients for the treatment of acute, symptomatic hypocalcemia.

Pediatric approval for calcium gluconate injection, including doses, is not based on adequate and well-controlled clinical studies. Safety and dosing recommendations in pediatric patients are based on published literature and clinical experience [see Dosage and Administration (2.2)].

Concomitant use of ceftriaxone and calcium gluconate injection is contraindicated in neonates (28 days of age or younger) due to reports of fatal outcomes associated with the presence of lung and kidney ceftriaxone-calcium precipitates. In patients older than 28 days of age, ceftriaxone and calcium gluconate injection may be administered sequentially, provided the infusion lines are thoroughly flushed between infusions with a compatible fluid [see Contraindications (4) and Warnings and Precautions (5.2)]. This product contains up to 25 mcg/L aluminum which may be toxic, particularly for premature neonates due to immature renal function. Parenteral administration of aluminum greater than 4 to 5 mcg/kg/day is associated with central nervous system and bone toxicity [see Warnings and Precautions (5.5)].

8.5 Geriatric Use

In general dose selection for an elderly patient should start at the lowest dose of the recommended dose range, reflecting the greater frequency of decreased hepatic, renal, or cardiac function, and of concomitant disease or other drug therapy.

8.6 Renal Impairment

For patients with renal impairment, initiate calcium gluconate injection at the lowest dose of the recommended dose ranges across all age groups. Monitor serum calcium levels every 4 hours [see Dosage and Administration (2.4)].

8.7 Hepatic Impairment

Hepatic function does not impact the availability of ionized calcium after calcium gluconate intravenous administration. Dose adjustment in hepatically impaired patients may not be necessary.

10 OVERDOSAGE

Overdosage of calcium gluconate injection may result in hypercalcemia. Symptoms of hypercalcemia typically develop when the total serum calcium concentration is ≥12 mg/dL. Neurologic symptoms include depression, weakness, fatigue, and confusion at lower levels, with patients experiencing hallucinations, disorientation, hypotonicity, seizures, and coma. Effects on the kidney include diminished ability to concentrate urine and diuresis.

If overdose of calcium gluconate injection occurs immediately discontinue administration and provide supportive treatments to restore intravascular volume as well as promote calcium excretion in the urine if necessary.

11 DESCRIPTION

Calcium Gluconate Injection is a sterile, preservative-free, nonpyrogenic, supersaturated solution of calcium gluconate, a form of calcium, for intravenous use after dilution.

Calcium Gluconate is calcium D-gluconate (1:2) monohydrate. The structural formula is:

Molecular formula: C12H22CaO14• H2O

Molecular weight: 448.39

Solubility in water: 3.5 g/100 mL at 25°C

Calcium Gluconate Injection is available as 10,000 mg per 100 mL (100 mg per mL) in a pharmacy bulk package (bag).

Each mL of Calcium Gluconate Injection contains 100 mg of calcium gluconate (equivalent to 94 mg of calcium gluconate anhydrous and 4.5 mg of calcium saccharate tetrahydrate), hydrochloric acid and/or sodium hydroxide for pH adjustment (6.0 to 8.2) and sterile water for injection, q.s. It contains no antimicrobial agent.

Each mL of Calcium Gluconate Injection contains 9.3 mg (0.465 mEq) of elemental calcium.

12 CLINICAL PHARMACOLOGY

12.1 Mechanism of Action

Intravenous administration of calcium gluconate increases serum ionized calcium level. Calcium gluconate dissociates into ionized calcium in plasma. Ionized calcium and gluconate are normal constituents of body fluids.

12.3 Pharmacokinetics

Absorption

Calcium gluconate injection is 100% bioavailable following intravenous injection.

Metabolism

Calcium itself does not undergo direct metabolism. The release of ionized calcium from intravenous administration of calcium gluconate is direct and does not seem to be affected by the first pass through the liver.

Distribution

Calcium in the body is distributed mainly in skeleton (99%). Only 1% of the total body calcium is distributed within the extracellular fluids and soft tissues. About 50% of total serum calcium is in the ionized form and represents the biologically active part. 8% to 10% serum calcium is bound to organic and inorganic acid and approximately 40% is protein-bound (primarily to albumin).

Elimination

Studies have shown a relationship between urinary calcium excretion and the intravenous administration of calcium gluconate, with a significant increase in urinary calcium excretion observed after the intravenous administration of calcium gluconate.

13 NONCLINICAL TOXICOLOGY

13.1 Carcinogenesis, Mutagenesis, Impairment of Fertility

Long-term studies in animals have not been conducted to evaluate the carcinogenic potential of calcium gluconate injection. Calcium gluconate was not mutagenic with or without metabolic activation in the Ames test with Salmonella typhimurium (strains TA-1535, TA-1537, and TA-1538) or Saccharomyces cerevisiae (Strain D4). Fertility studies in animals have not been conducted with calcium gluconate administered by the intravenous route.

16 HOW SUPPLIED/STORAGE AND HANDLING

Calcium Gluconate Injection is a clear, colorless solution supplied in a 100 mL Pharmacy Bulk Package (bag) in an aluminum overwrap available as:

Calcium Gluconate Total Product Strength (Concentration) | Carton Configuration | Carton NDC | Bag and Overwrap NDC
10,000 mg calcium gluconate per; 100 mL (100 mg per mL) | Carton containing ten 100 mL pharmacy bulk package | 44567-623-10 | 44567-623-01

Store at 20°C to 25°C (68°F to 77°F) [see USP Controlled Room Temperature]. Do not freeze.

Preservative Free. Sterile. Protect from light until use. Discard any unused portion in the Pharmacy Bulk Package within 4 hours after initial closure puncture.

Each dose dispensed from the Pharmacy Bulk Package must be used immediately.

The diluted solution must be used immediately.

Supersaturated solutions are prone to precipitation. The precipitate, if present, may be dissolved by warming to 60°C to 80°C, with occasional agitation, until the solution becomes clear. Shake vigorously. Allow to cool to room temperature before dispensing. Use injection only if clear immediately prior to use.

17 PATIENT COUNSELING INFORMATION

Advise the patient that the risks associated with infusion including local tissue inflammation, local necrosis and calcinosis [see Warnings and Precautions (5.3)].

Manufactured for:

WG Critical Care, LLC

Paramus, NJ 07652

Made in Switzerland

PACKAGE/LABEL PRINCIPAL DISPLAY PANEL

NDC 44567-623-01

Calcium Gluconate Injection 10,000 mg per 100 mL (100 mg/mL)